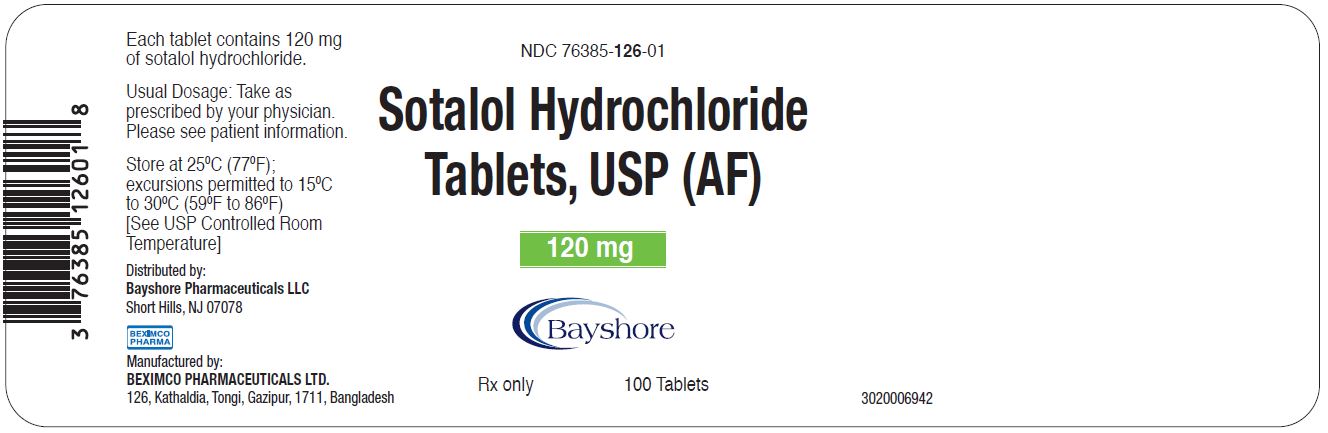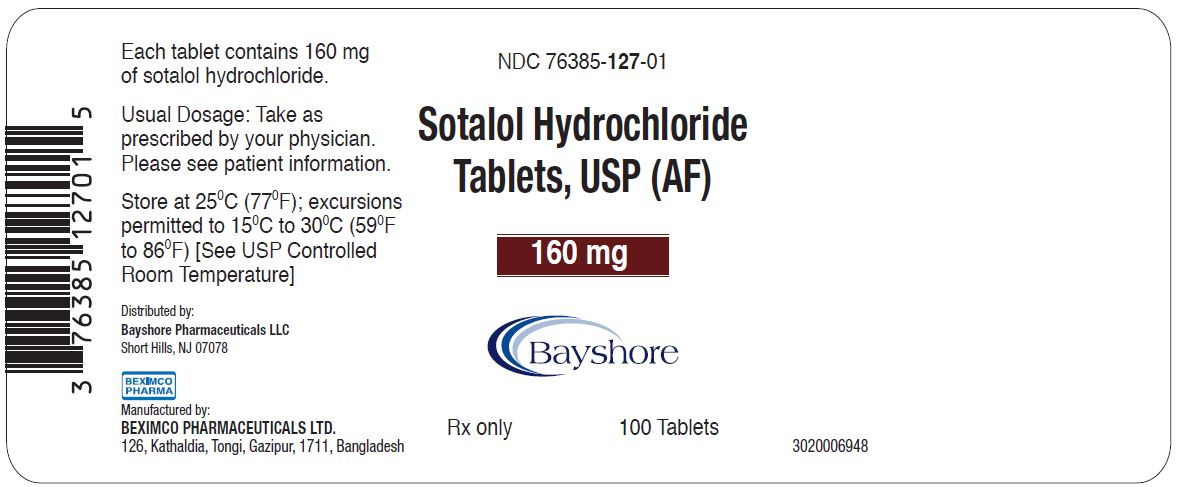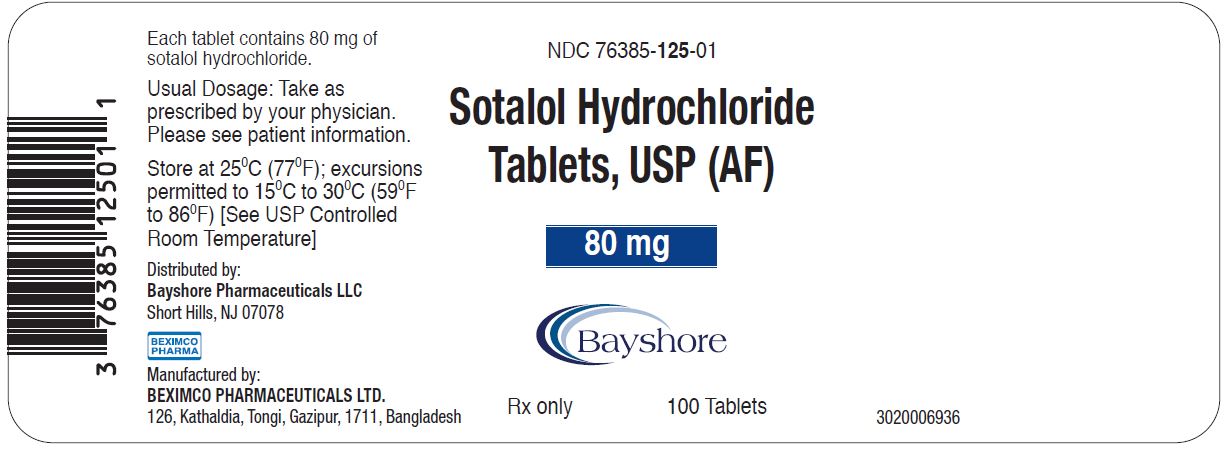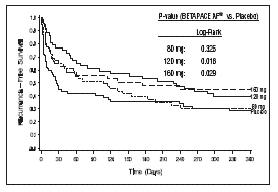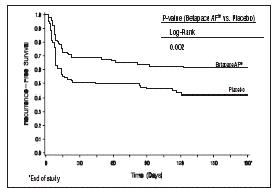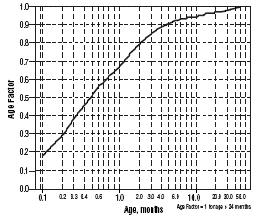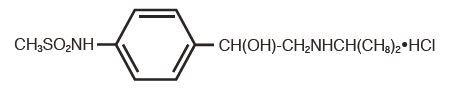 DRUG LABEL: Sotalol Hydrochloride
NDC: 76385-125 | Form: TABLET
Manufacturer: Bayshore Pharmaceuticals LLC
Category: prescription | Type: HUMAN PRESCRIPTION DRUG LABEL
Date: 20240117

ACTIVE INGREDIENTS: SOTALOL HYDROCHLORIDE 80 mg/1 1
INACTIVE INGREDIENTS: CELLULOSE, MICROCRYSTALLINE; LACTOSE MONOHYDRATE; STARCH, CORN; STEARIC ACID; MAGNESIUM STEARATE; SILICON DIOXIDE

Sotalol Hydrochloride Tablets, USP (AF) 80 mg, 120 mg, and 160 mg

BOXED WARNING

To minimize the risk of induced arrhythmia, patients initiated or re-initiated on Sotalol Hydrochloride Tablets (AF) should be placed for a minimum of three days (on their maintenance dose) in a facility that can provide cardiac resuscitation, continuous electrocardiographic monitoring and calculations of creatinine clearance. For detailed instructions regarding dose selection, and special cautions for people with renal impairment, see DOSAGE AND ADMINISTRATION. Sotalol is also indicated for the treatment of documented life threatening ventricular arrhythmias and is marketed under the brand name Betapace® (sotalol hydrochloride tablets). Sotalol hydrochloride tablets, however, should not be substituted for sotalol hydrochloride tablets (AF) because of significant differences in labeling (i.e., patient package insert, dosing administration and safety information).

Rx only

DESCRIPTION

Sotalol Hydrochloride Tablets, USP (AF) is an antiarrhythmic drug with Class II (beta-adrenoreceptor blocking) and Class III (cardiac action potential duration prolongation) properties. It is supplied as a white, capsule-shaped tablet for oral administration. Sotalol hydrochloride is a white, crystalline solid with a molecular weight of 308.8. It is hydrophilic, soluble in water, propylene glycol and ethanol, but is only slightly soluble in chloroform. Chemically, sotalol hydrochloride is d,l-N-[4-[1-hydroxy-2-[(1-methylethyl)amino]ethyl]phenyl]methanesulfonamide monohydrochloride. The molecular formula is C12H20N2O3 S•HCl and is represented by the following structural formula:

Sotalol Hydrochloride Tablets, USP (AF) contain the following inactive ingredients: microcrystalline cellulose, lactose monohydrate, pregelatinized starch, stearic acid, magnesium stearate and colloidal silicon dioxide.

CLINICAL PHARMACOLOGY

Mechanism of Action

Sotalol AF has both beta-adrenoreceptor blocking (Vaughan Williams Class II) and cardiac action potential duration prolongation (Vaughan Williams Class III) antiarrhythmic properties. Sotalol AF is a racemic mixture of dand l-sotalol. Both isomers have similar Class III antiarrhythmic effects, while the l-isomer is responsible for virtually all of the beta-blocking activity. The beta-blocking effect of sotalol is non-cardioselective, half maximal at about 80 mg/day and maximal at doses between 320 and 640 mg/day. Sotalol does not have partial agonist or membrane stabilizing activity. Although significant beta-blockade occurs at oral doses as low as 25 mg, significant Class III effects are seen only at daily doses of 160 mg and above.

In children, a Class III electrophysiological effect can be seen at daily doses of 210 mg/m^2 body surface area (BSA). A reduction of the resting heart rate due to the beta-blocking effect of sotalol is observed at daily doses ≥90 mg/m^2 in children.

Electrophysiology

Sotalol hydrochloride prolongs the plateau phase of the cardiac action potential in the isolated myocyte, as well as in isolated tissue preparations of ventricular or atrial muscle (Class III activity). In intact animals it slows heart rate, decreases AV nodal conduction and increases the refractory periods of atrial and ventricular muscle and conduction tissue.

In man, the Class II (beta-blockade) electrophysiological effects of Sotalol AF are manifested by increased sinus cycle length (slowed heart rate), decreased AV nodal conduction and increased AV nodal refractoriness. The Class III electrophysiological effects in man include prolongation of the atrial and ventricular monophasic action potentials, and effective refractory period prolongation of atrial muscle, ventricular muscle, and atrio-ventricular accessory pathways (where present) in both the anterograde and retrograde directions. With oral doses of 160 to 640 mg/day, the surface ECG shows dose-related mean increases of 40 to 100 msec in QTc and 10 to 40 msec in QTc. In a study of patients with atrial fibrillation (AFIB)/flutter (AFIB/AFL) receiving three different oral doses of Sotalol AF given q12h (or q24h in patients with a reduced creatinine clearance), mean increases in QT intervals measured from 12-lead ECGs of 25 msec, 40 msec and 54 msec were found in the 80 mg, 120 mg, and 160 mg dose groups, respectively. (See WARNINGS for description of relationship between QTc and Torsade de Pointes type arrhythmias.) No significant alteration in QRS interval is observed.

In a small study (n=25) of patients with implanted defibrillators treated concurrently with sotalol, the average defibrillatory threshold was 6 joules (range 2 to 15 joules) compared to a mean of 16 joules for a non-randomized comparative group primarily receiving amiodarone.

In a dose-response trial comparing three dose levels of Sotalol AF, 80 mg, 120 mg, and 160 mg with placebo given q12h (or q24h in patients with a reduced renal creatinine clearance) for the prevention of recurrence of symptomatic atrial fibrillation (AFIB)/flutter (AFL), the mean ventricular rate during recurrence of AFIB/AFL was 125, 107, 110 and 99 beats/min in the placebo, 80 mg, 120 mg and 160 mg dose groups, respectively (p<0.017 for each sotalol dose group versus placebo). In another placebo controlled trial in which Sotalol AF was titrated to a dose between 160 and 320 mg/day in patients with chronic AFIB, the mean ventricular rate during recurrence of AFIB was 107 and 84 beats/min in the placebo and Sotalol AF groups, respectively (p<0.001).

Twenty-five children in an unblinded, multicenter trial with supraventricular (SVT) and/or ventricular (VT) tachyarrhythmias, aged between 3 days and 12 years (mostly neonates and infants), received an ascending titration regimen with daily doses of 30, 90 and 210 mg/m^2 with dosing every 8 hours for a total of 9 doses. During steady-state, the respective average increases above baseline of the QTc interval, in msec (%), were 2(+1%), 14(+4%) and 29(+7%) msec at the 3 dose levels. The respective mean maximum increases above baseline of the QTc interval, in msec (%), were 23(+6%), 36(+9%) and 55(+14%) msec at the 3 dose levels. The steady-state percent increases in the RR interval were 3, 9 and 12%. The smallest children (BSA<0.33m^2) showed a tendency for larger Class III effects (ΔQTc) and an increased frequency of prolongations of the QTc interval as compared with the larger children (BSA≥.0.33m^2). The beta-blocking effects also tended to be greater in the smaller children (BSA<0.33m^2). Both the Class III and beta-blocking effects of sotalol were linearly related with the plasma concentrations.

Hemodynamics

In a study of systemic hemodynamic function measured invasively in 12 patients with a mean LV ejection fraction of 37% and ventricular tachycardia (9 sustained and 3 non-sustained), a median dose of 160 mg twice daily of sotalol produced a 28% reduction in heart rate and a 24% decrease in cardiac index at 2 hours post dosing at steady-state. Concurrently, systemic vascular resistance and stroke volume showed non-significant increases of 25% and 8%, respectively. Pulmonary capillary wedge pressure increased significantly from 6.4 mmHg to 11.8 mmHg in the 11 patients who completed the study. One patient was discontinued because of worsening congestive heart failure. Mean arterial pressure, mean pulmonary artery pressure and stroke work index did not significantly change. Exercise and isoproterenol induced tachycardia are antagonized by sotalol, and total peripheral resistance increases by a small amount.

In hypertensive patients, sotalol produces significant reductions in both systolic and diastolic blood pressures. Although sotalol is usually well-tolerated hemodynamically, caution should be exercised in patients with marginal cardiac compensation as deterioration in cardiac performance may occur. (See WARNINGS: Congestive Heart Failure.)

Clinical Studies

Prolongation of Time to Recurrence of Symptomatic Atrial Fibrillation/ Flutter

Sotalol AF has been studied in patients with symptomatic AFIB/AFL in two principal studies, one in patients with primarily paroxysmal AFIB/AFL, the other in patients with primarily chronic AFIB.

In one study, a U.S. multicenter, randomized, placebo-controlled, double-blind, dose-response trial of patients with symptomatic primarily paroxysmal AFIB/AFL, three fixed dose levels of Sotalol AF (80 mg, 120 mg and 160 mg) twice daily and placebo were compared in 253 patients. In patients with reduced creatinine clearance (40 to 60 mL/min) the same doses were given once daily. Patients were not randomized for the following reasons: QT >450 msec; creatinine clearance <40 mL/min; intolerance to beta-blockers; bradycardia-tachycardia syndrome in the absence of an implanted pacemaker; AFIB/AFL was asymptomatic or was associated with syncope, embolic CVA or TIA; acute myocardial infarction within the previous 2 months; congestive heart failure; bronchial asthma or other contraindications to beta-blocker therapy; receiving potassium losing diuretics without potassium replacement or without concurrent use of ACE-inhibitors; uncorrected hypokalemia (serum potassium <3.5 meq/L) or hypomagnesemia (serum magnesium <1.5 meq/L); received chronic oral amiodarone therapy for >1 month within previous 12 weeks; congenital or acquired long QT syndromes; history of Torsade de Pointes with other antiarrhythmic agents which increase the duration of ventricular repolarization; sinus rate <50 bpm during waking hours; unstable angina pectoris; receiving treatment with other drugs that prolong the QT interval; and AFIB/AFL associated with the Wolff-Parkinson-White (WPW) syndrome. If the QT interval increased to ≥520 msec (or JT ≥430 msec if QRS >100 msec) the drug was discontinued. The patient population in this trial was 64% male, and the mean age was 62 years. No structural heart disease was present in 43% of the patients. Doses were administered once daily in 20% of the patients because of reduced creatinine clearance.

Sotalol AF was shown to prolong the time to the first symptomatic, ECG-documented recurrence of AFIB/AFL, as well as to reduce the risk of such recurrence at both 6 and 12 months. The 120 mg dose was more effective than 80 mg, but 160 mg did not appear to have an added benefit. Note that these doses were given twice or once daily, depending on renal function. The results are shown in Figure 1 and Tables 1 and 2.

Figure 1 Study 1—Time to First ECG-Documented Recurrence of Symptomatic AFIB/AFL Since Randomization

Table 1 Study 1—Patient Status at 12 Months
 | Placebo | Sotalol AF Dose
 | Placebo | 80 mg | 120 mg | 160 mg
Randomized | 69 | 59 | 63 | 62
On treatment in NSR; at 12 months; without recurrence [Symptomatic AFIB/AFL] | 23% | 22% | 29% | 23%
Recurrence [Efficacy endpoint of Study 1; study treatment stopped.] | 67% | 58% | 49% | 42%
D/C for AEs | 6% | 12% | 18% | 29%

Please note that columns do not add up to 100% due to discontinuations (D/C) for "other" reasons.

Table 2 Study 1—Median Time to Recurrence of Symptomatic AFIB/AFL and Relative Risk (vs. Placebo) at 12 Months
 | Placebo | Sotalol AF Dose
 | Placebo | 80 mg | 120 mg | 160 mg
p-value vs placebo |  | p=0.325 | p=0.018 | p=0.029
Relative Risk (RR); to placebo |  | 0.81 | 0.59 | 0.59
Median time to; recurrence (days) | 27 | 106 | 229 | 175
Discontinuation because of adverse events was dose related.

In a second multicenter, randomized, placebo-controlled, double-blind study of 6 months duration in 232 patients with chronic AFIB, Sotalol AF was titrated over a dose range from 80 mg/day to 320 mg/day. The patient population of this trial was 70% male with a mean age of 65 years. Structural heart disease was present in 49% of the patients. All patients had chronic AFIB for >2 weeks but <1 year at entry with a mean duration of 4.1 months. Patients were excluded if they had significant electrolyte imbalance, QTc >460 msec, QRS >140 msec, any degree of AV block or functioning pacemaker, uncompensated cardiac failure, asthma, significant renal disease (estimated creatinine clearance <50 mL/min), heart rate <50 bpm, myocardial infarction or open heart surgery in past 2 months, unstable angina, infective endocarditis, active pericarditis or myocarditis, ≥ 3 DC cardioversions in the past, medications that prolonged QT interval, and previous amiodarone treatment. After successful cardioversion patients were randomized to receive placebo (n=114) or Sotalol AF (n=118), at a starting dose of 80 mg twice daily. If the initial dose was not tolerated it was decreased to 80 mg once daily, but if it was tolerated it was increased to 160 mg twice daily. During the maintenance period 67% of treated patients received a dose of 160 mg twice daily, and the remainder received doses of 80 mg once daily (17%) and 80 mg twice daily (16%).

Figure 2 and Tables 3 and 4 show the results of the trial. There was a longer time to ECG-documented recurrence of AFIB and a reduced risk of recurrence at 6 months compared to placebo.

Figure 2 Study 2 – Time to First ECG-Documented Recurrence of Symptomatic AFIB/AFL/Death Since Randomization

Table 3 Study 2—Patient Status at 6 Months
 | Sotalol AF | Placebo
Randomized | 118 | 114
On treatment in NSR at 6 months without recurrence [Symptomatic or asymptomatic AFIB/AFL] | 45% | 29%
Recurrence [Efficacy endpoint of Study 2; study treatment stopped.] | 49% | 67%
D/C for AEs | 6% | 3%
Death |  | 1%

Table 4 Study 2—Median Time to Recurrence of Symptomatic AFIB/AFL/Death and Relative Risk (vs. Placebo) at 6 Months
 | Sotalol AF | Placebo
p-value vs placebo | p=0.002
Relative Risk (RR) to placebo | 0.55
Median time to recurrence (days) | >180 | 44

Safety in Patients with Structural Heart Disease

In a multicenter double-blind randomized study reported by D. Julian et al, the effect of sotalol 320 mg once daily was compared with that of placebo in 1456 patients (randomized 3:2, sotalol to placebo) surviving an acute myocardial infarction (MI). Treatment was started 5 to 14 days after infarction. Patients were followed for 12 months. The mortality rate was 7.3% in the sotalol group and 8.9% in the placebo group, not a statistically significant difference. Although the results do not show evidence of a benefit of sotalol in this population, they do not show an added risk in post MI patients receiving sotalol.

Pharmacokinetics

In healthy subjects, the oral bioavailability of sotalol is 90 to 100%. After oral administration, peak plasma concentrations are reached in 2.5 to 4 hours, and steady-state plasma concentrations are attained within 2 to 3 days (i.e., after 5 to 6 doses when administered twice daily). Over the dosage range 160 to 640 mg/day sotalol displays dose proportionality with respect to plasma concentrations. Distribution occurs to a central (plasma) and to a peripheral compartment, with a mean elimination half-life of 12 hours. Dosing every 12 hours results in trough plasma concentrations which are approximately one-half of those at peak.

Sotalol does not bind to plasma proteins and is not metabolized. Sotalol shows very little intersubject variability in plasma levels. The pharmacokinetics of the d and l enantiomers of sotalol are essentially identical. Sotalol crosses the blood brain barrier poorly. Excretion is predominantly via the kidney in the unchanged form, and therefore lower doses are necessary in conditions of renal impairment (see DOSAGE AND ADMINISTRATION). Age per se does not significantly alter the pharmacokinetics of sotalol, but impaired renal function in geriatric patients can increase the terminal elimination half-life, resulting in increased drug accumulation. The absorption of sotalol was reduced by approximately 20% compared to fasting when it was administered with a standard meal. Since sotalol is not subject to first-pass metabolism, patients with hepatic impairment show no alteration in clearance of sotalol.

The combined analysis of two unblinded, multicenter trials (a single dose and a multiple dose study) with 59 children, aged between 3 days and 12 years, showed the pharmacokinetics of sotalol to be first order. A daily dose of 30 mg/m^2 of sotalol was administered in the single dose study and daily doses of 30, 90 and 210 mg/m^2 were administered q8h in the multi-dose study. After rapid absorption with peak levels occurring on average between 2 to 3 hours following administration, sotalol was eliminated with a mean half-life of 9.5 hours. Steady-state was reached after 1 to 2 days. The average peak to trough concentration ratio was 2. BSA was the most important covariate and more relevant than age for the pharmacokinetics of sotalol. The smallest children (BSA <0.33m^2) exhibited a greater drug exposure (+59%) than the larger children who showed a uniform drug concentration profile. The intersubject variation for oral clearance was 22%.

INDICATIONS AND USAGE

Sotalol AF are indicated for the maintenance of normal sinus rhythm [delay in time to recurrence of atrial fibrillation/atrial flutter (AFIB/AFL)] in patients with symptomatic AFIB/AFL who are currently in sinus rhythm. Because Sotalol AF can cause life-threatening ventricular arrhythmias, it should be reserved for patients in whom AFIB/AFL is highly symptomatic. Patients with paroxysmal AFIB whose AFIB/AFL that is easily reversed (by Valsalva maneuver, for example) should usually not be given Sotalol AF (see WARNINGS).

In general, antiarrhythmic therapy for AFIB/AFL aims to prolong the time in normal sinus rhythm. Recurrence is expected in some patients (see Clinical Studies).

Sotalol is also indicated for the treatment of documented life-threatening ventricular arrhythmias and is marketed under the brand name Betapace® (sotalol hydrochloride). Sotalol hydrochloride tablets, however, must not be substituted for sotalol hydrochloride tablets (AF) because of significant differences in labeling (i.e., patient package insert, dosing administration and safety information).

CONTRAINDICATIONS

Sotalol AF is contraindicated in patients with sinus bradycardia (<50 bpm during waking hours), sick sinus syndrome or second and third degree AV block (unless a functioning pacemaker is present), congenital or acquired long QT syndromes, baseline QT interval >450 msec, cardiogenic shock, uncontrolled heart failure, hypokalemia (<4 meq/L), creatinine clearance <40 mL/min, bronchial asthma and previous evidence of hypersensitivity to sotalol.

WARNINGS

Ventricular Arrhythmia

Sotalol AF can cause serious ventricular arrhythmias, primarily Torsade de Pointes (TdP) type ventricular tachycardia, a polymorphic ventricular tachycardia associated with QT interval prolongation. QT interval prolongation is directly related to the dose of Sotalol AF. Factors such as reduced creatinine clearance, gender (female) and larger doses increase the risk of TdP. The risk of TdP can be reduced by adjustment of the Sotalol AF dose according to creatinine clearance and by monitoring the ECG for excessive increases in the QT interval.

Treatment with Sotalol AF must therefore be started only in patients observed for a minimum of three days on their maintenance dose in a facility that can provide electrocardiographic monitoring and in the presence of personnel trained in the management of serious ventricular arrhythmias. Calculation of the creatinine clearance must precede administration of the first dose of Sotalol AF. For detailed instructions regarding dose selection, see DOSAGE AND ADMINISTRATION.

Proarrhythmia in Atrial Fibrillation/Atrial Flutter Patients

In eight controlled trials of patients with AFIB/AFL and other supraventricular arrhythmias (N=659) there were four cases of Torsade de Pointes reported (0.6%) during the controlled phase of treatment with Sotalol AF. The incidence of Torsade de Pointes was significantly lower in those patients receiving total daily doses of 320 mg or less (0.3%), as summarized in Table 5 below. Both patients who had Torsade de Pointes in the group receiving >320 mg/day were receiving 640 mg/day. In the group receiving ≤320 mg daily, one case of TdP occurred at a daily dose of 320 mg on day 4 of treatment and one case occurred on a daily dose of 160 mg on day 1 of treatment.

Table 5 Incidence of Torsade de Pointes in Controlled Trials of AFIB and Other Supraventricular Arrhythmias
 | Sotalol AF (Daily Dose)
 | Any; Dose; (N=659) | >320; mg/day; (N=62) | ≤320; mg/day; (N=597) | ≤240; mg/day; (N=340) | Placebo; (N=358)
 | n(%) | n(%) | n(%) | n(%) | n(%)
Torsade de Pointes | 4(0.6%) | 2(3.2%) | 2(0.3%) | 1(0.3%) | 0

Prolongation of the QT interval is dose related, increasing from baseline an average of 25, 40, and 50 msec in the 80, 120, and 160 mg groups, respectively, in the clinical dose-response study. In this clinical trial Sotalol AF treatment was not initiated if the QT interval was greater than 450 msec and during therapy the dose was reduced or discontinued if the QT interval was ≥520 msec.

Experience in patients with ventricular arrhythmias is also pertinent to the risk of Torsade de Pointes in patients with AFIB/AFL (see below).

Proarrhythmia in Ventricular Arrhythmia Patients: [see Sotalol (sotalol hydrochloride) Package Insert]

In patients with a history of sustained ventricular tachycardia, the incidence of Torsade de Pointes during sotalol treatment was 4% and worsened VT in about 1%; in patients with other less serious ventricular arrhythmias the incidence of Torsade de Pointes was 1% and new or worsened VT in about 0.7%. Additionally, in approximately 1% of patients, deaths were considered possibly drug related; such cases, although difficult to evaluate, may have been associated with proarrhythmic events.

Torsade de Pointes arrhythmias in patients with VT/VF were dose related, as was the prolongation of QT (QTc) interval, as shown in Table 6 below.

Table 6 Percent Incidence of Torsade de Pointes and Mean QTc Interval by Dose For Patients With Sustained VT/VF
Daily Dose (mg) | Incidence of Torsade de Pointes | Mean QTc [highest on-therapy value] (msec)
80 | 0 (69) [() Number of patients assessed] | 463 (17)
160 | 0.5 (832) | 467 (181)
320 | 1.6 (835) | 473 (344)
480 | 4.4 (459) | 483 (234)
640 | 3.7 (324) | 490 (185)
>640 | 5.8 (103) | 512 (62)

Table 7 below relates the incidence of Torsade de Pointes to on-therapy QTc and change in QTc from baseline. It should be noted, however, that the highest on therapy QTc was in many cases the one obtained at the time of the Torsade de Pointes event, so that the table overstates the predictive value of a high QTc.

Table 7 Relationship Between QTc Interval Prolongation and Torsade de Pointes
On-Therapy; QTc Interval; (msec) | Incidence of; Torsade de; Pointes | Change in QTc; Interval From; Baseline (msec) | Incidence of; Torsade de; Pointes
less than 500 | 1.3% (1787) [() Number of patients assessed] | less than 65 | 1.6% (1516)
500 to 525 | 3.4% (236) | 65 to 80 | 3.2% (158)
525 to 550 | 5.6% (125) | 80 to 100 | 4.1% (146)
>550 | 10.8% (157) | 100 to 30 | 5.2% (115)
 |  | >130 | 7.1% (99)

In addition to dose and presence of sustained VT, other risk factors for Torsade de Pointes were gender (females had a higher incidence), excessive prolongation of the QTc interval and history of cardiomegaly or congestive heart failure. Patients with sustained ventricular tachycardia and a history of congestive heart failure appear to have the highest risk for serious proarrhythmia (7%). Of the ventricular arrhythmia patients experiencing Torsade de Pointes, approximately two-thirds spontaneously reverted to their baseline rhythm. The others were either converted electrically (D/C cardioversion or overdrive pacing) or treated with other drugs (see OVERDOSAGE). It is not possible to determine whether some sudden deaths represented episodes of Torsade de Pointes, but in some instances sudden death did follow a documented episode of Torsade de Pointes. Although sotalol therapy was discontinued in most patients experiencing Torsade de Pointes, 17% were continued on a lower dose.

Use with Drugs that Prolong QT Interval and Antiarrhythmic Agents

The use of Sotalol AF in conjunction with other drugs that prolong the QT interval has not been studied and is not recommended. Such drugs include many antiarrhythmics, some phenothiazines, bepridil, tricyclic antidepressants, and certain oral macrolides. Class I or Class III antiarrhythmic agents should be withheld for at least three half-lives prior to dosing with Sotalol AF. In clinical trials, Sotalol AF was not administered to patients previously treated with oral amiodarone for >1 month in the previous three months. Class Ia antiarrhythmic drugs, such as disopyramide, quinidine and procainamide and other Class III drugs (e.g., amiodarone) are not recommended as concomitant therapy with Sotalol AF because of their potential to prolong refractoriness (see WARNINGS). There is only limited experience with the concomitant use of Class Ib or Ic antiarrhythmics.

Congestive Heart Failure

Sympathetic stimulation is necessary in supporting circulatory function in congestive heart failure, and beta-blockade carries the potential hazard of further depressing myocardial contractility and precipitating more severe failure. In patients who have heart failure controlled by digitalis and/or diuretics, Sotalol AF should be administered cautiously. Both digitalis and sotalol slow AV conduction. As with all beta-blockers, caution is advised when initiating therapy in patients with any evidence of left ventricular dysfunction. In a pooled data base of four placebo-controlled AFIB/AFL and PSVT studies, new or worsening CHF occurred during therapy with Sotalol AF in 5 (1.2%) of 415 patients. In these studies patients with uncontrolled heart failure were excluded (i.e., NYHA Functional Classes III or IV). In other premarketing sotalol studies, new or worsened congestive heart failure (CHF) occurred in 3.3% (n=3257) of patients and led to discontinuation in approximately 1% of patients receiving sotalol. The incidence was higher in patients presenting with sustained ventricular tachycardia/fibrillation (4.6%, n=1363), or a prior history of heart failure (7.3%, n=696). Based on a life-table analysis, the one-year incidence of new or worsened CHF was 3% in patients without a prior history and 10% in patients with a prior history of CHF. NYHA Classification was also closely associated to the incidence of new or worsened heart failure while receiving sotalol (1.8% in 1395 Class I patients, 4.9% in 1254 Class II patients and 6.1% in 278 Class III or IV patients).

Electrolyte Disturbances

Sotalol AF should not be used in patients with hypokalemia or hypomagnesemia prior to correction of imbalance, as these conditions can exaggerate the degree of QT prolongation, and increase the potential for Torsade de Pointes. Special attention should be given to electrolyte and acid-base balance in patients experiencing severe or prolonged diarrhea or patients receiving concomitant diuretic drugs.

Bradycardia/Heart Block

The incidence of bradycardia (as determined by the investigators) in the supraventricular arrhythmia population treated with Sotalol AF (N = 415) was 13%, and led to discontinuation in 2.4% of patients. Bradycardia itself increases the risk of Torsade de Pointes.

Recent Acute MI

Sotalol has been used in a controlled trial following an acute myocardial infarction without evidence of increased mortality (see Safety in Patients with Structural Heart Disease). Although specific studies of its use in treating atrial arrhythmias after infarction have not been conducted, the usual precautions regarding heart failure, avoidance of hypokalemia, bradycardia or prolonged QT interval apply.

Abrupt Withdrawal

Hypersensitivity to catecholamines has been observed in patients withdrawn from beta-blocker therapy. Occasional cases of exacerbation of angina pectoris, arrhythmias and, in some cases, myocardial infarction have been reported after abrupt discontinuation of beta-blocker therapy. Therefore, it is prudent when discontinuing chronically administered Sotalol AF, particularly in patients with ischemic heart disease, to carefully monitor the patient and consider the temporary use of an alternate beta-blocker if appropriate. If possible, the dosage of Sotalol AF should be gradually reduced over a period of one to two weeks. If angina or acute coronary insufficiency develops, appropriate therapy should be instituted promptly. Patients should be warned against interruption or discontinuation of therapy without the physician's advice. Because coronary artery disease is common and may be unrecognized in patients receiving Sotalol AF, abrupt discontinuation in patients with arrhythmias may unmask latent coronary insufficiency.

Non-Allergic Bronchospasm (e.g., chronic bronchitis and emphysema)

PATIENTS WITH BRONCHOSPASTIC DISEASES SHOULD IN GENERAL NOT RECEIVE BETA-BLOCKERS. It is prudent, if Sotalol AF (sotalol hydrochloride) is to be administered, to use the smallest effective dose, so that inhibition of bronchodilation produced by endogenous or exogenous catecholamine stimulation of beta2 receptors may be minimized.

Anaphylaxis

While taking beta-blockers, patients with a history of anaphylactic reaction to a variety of allergens may have a more severe reaction on repeated challenge, either accidental, diagnostic or therapeutic. Such patients may be unresponsive to the usual doses of epinephrine used to treat the allergic reaction.

Major Surgery

Chronically administered beta-blocking therapy should not be routinely withdrawn prior to major surgery, however the impaired ability of the heart to respond to reflex adrenergic stimuli may augment the risks of general anesthesia and surgical procedures.

Diabetes

In patients with diabetes (especially labile diabetes) or with a history of episodes of spontaneous hypoglycemia, Sotalol AF should be given with caution since beta-blockade may mask some important premonitory signs of acute hypoglycemia; e.g., tachycardia.

Sick Sinus Syndrome

Sotalol AF should be used only with extreme caution in patients with sick sinus syndrome associated with symptomatic arrhythmias, because it may cause sinus bradycardia, sinus pauses or sinus arrest. In patients with AFIB and sinus node dysfunction, the risk of Torsade de Pointes with Sotalol AF therapy is increased, especially after cardioversion. Bradycardia following cardioversion in these patients is associated with QTc interval prolongation which is augmented due to the reverse use dependence of the Class III effects of Sotalol AF. Patients with AFIB/AFL associated with the sick sinus syndrome may be treated with Sotalol AF if they have an implanted pacemaker for control of bradycardia symptoms.

Thyrotoxicosis

Beta-blockade may mask certain clinical signs (e.g., tachycardia) of hyperthyroidism. Patients suspected of developing thyrotoxicosis should be managed carefully to avoid abrupt withdrawal of beta-blockade which might be followed by an exacerbation of symptoms of hyperthyroidism, including thyroid storm. The beta-blocking effects of Sotalol AF may be useful in controlling heart rate in AFIB associated with thyrotoxicosis but no study has been conducted to evaluate this.

PRECAUTIONS

Renal Impairment

Sotalol AF is eliminated principally via the kidneys through glomerular filtration and to a small degree by tubular secretion. There is a direct relationship between renal function, as measured by serum creatinine or creatinine clearance, and the elimination rate of Sotalol AF. Guidance for dosing in conditions of renal impairment can be found under DOSAGE AND ADMINISTRATION.

Information for Patients

Please refer to the patient package insert.

Prior to initiation of Sotalol AF therapy, the patient should be advised to read the patient package insert and reread it each time therapy is renewed. The patient should be fully instructed on the need for compliance with the recommended dosing of Sotalol AF, the potential interactions with drugs that prolong the QT interval and other antiarrhythmics, and the need for periodic monitoring of QT and renal function to minimize the risk of serious abnormal rhythms.

Medications and Supplements

Assessment of patients' medication history should include all over-counter, prescription and herbal/natural preparations with emphasis on preparations that may affect the pharmacodynamics of Sotalol AF such as other cardiac antiarrhythmic drugs, some phenothiazines, bepridil, tricyclic antidepressants and oral macrolides (see WARNINGS and Use with Drugs that Prolong QT Interval and Antiarrhythmic Agents). Patients should be instructed to notify their health care providers of any change in over-the-counter, prescription or supplement use. If a patient is hospitalized or is prescribed a new medication for any condition, the patient must inform the health care provider of ongoing Sotalol AF therapy. Patients should also check with their health care provider and/or pharmacist prior to taking a new over-the-counter medicine.

Electrolyte Imbalance

If patients experience symptoms that may be associated with altered electrolyte balance, such as excessive or prolonged diarrhea, sweating, or vomiting, or loss of appetite or thirst, these conditions should be immediately reported to their health care provider.

Dosing Schedule

Patients should be instructed NOT to double the next dose if a dose is missed. The next dose should be taken at the usual time.

Drug Interactions

Drugs undergoing CYP450 metabolism

Sotalol is primarily eliminated by renal excretion; therefore, drugs that are metabolized by CYP450 are not expected to alter the pharmacokinetics of sotalol.

Digoxin

Proarrhythmic events were more common in sotalol treated patients also receiving digoxin; it is not clear whether this represents an interaction or is related to the presence of CHF, a known risk factor for proarrhythmia, in the patients receiving digoxin. Both digitalis glycosides and beta-blockers slow atrioventricular conduction and decrease heart rate. Concomitant use can increase the risk of bradycardia.

Calcium blocking drugs

Sotalol AF should be administered with caution in conjunction with calcium blocking drugs because of possible additive effects on atrioventricular conduction or ventricular function. Additionally, concomitant use of these drugs may have additive effects on blood pressure, possibly leading to hypotension.

Catecholamine-depleting agents

Concomitant use of catecholamine-depleting drugs, such as reserpine and guanethidine, with a beta-blocker may produce an excessive reduction of resting sympathetic nervous tone. Patients treated with Sotalol AF plus a catecholamine depletor should therefore be closely monitored for evidence of hypotension and/or marked bradycardia which may produce syncope.

Insulin and oral antidiabetics

Hyperglycemia may occur, and the dosage of insulin or antidiabetic drugs may require adjustment. Symptoms of hypoglycemia may be masked.

Beta-2-receptor stimulants

Beta-agonists such as salbutamol, terbutaline and isoprenaline may have to be administered in increased dosages when used concomitantly with Sotalol AF.

Clonidine

Beta-blocking drugs may potentiate the rebound hypertension sometimes observed after discontinuation of clonidine; therefore, caution is advised when discontinuing clonidine in patients receiving Sotalol AF.

Other

No pharmacokinetic interactions were observed with hydrochlorothiazide or warfarin.

Antacids

Administration of Sotalol AF within 2 hours of antacids containing aluminum oxide and magnesium hydroxide should be avoided because it may result in a reduction in Cmax and AUC of 26% and 20%, respectively and consequently in a 25% reduction in the bradycardic effect at rest. Administration of the antacid two hours after Sotalol AF has no effect on the pharmacokinetics or pharmacodynamics of sotalol.

Drug/Laboratory Test Interactions

The presence of sotalol in the urine may result in falsely elevated levels of urinary metanephrine when measured by fluorimetric or photometric methods. In screening patients suspected of having a pheochromocytoma and being treated with sotalol, a specific method, such as a high performance liquid chromatographic assay with solid phase extraction (e.g., J. Chromatogr. 385:241, 1987) should be employed in determining levels of catecholamines.

Carcinogenesis, Mutagenesis, Impairment of Fertility

No evidence of carcinogenic potential was observed in rats during a 24-month study at 137 to 275 mg/kg/ day (approximately 30 times the maximum recommended human oral dose (MRHD) as mg/kg or 5 times the MRHD as mg/m^2) or in mice, during a 24-month study at 4141 to 7122 mg/kg/day (approximately 450 to 750 times the MRHD as mg/kg or 36 to 63 times the MRHD as mg/m^2).

Sotalol has not been evaluated in any specific assay of mutagenicity or clastogenicity.

No significant reduction in fertility occurred in rats at oral doses of 1000 mg/kg/ day (approximately 100 times the MRHD as mg/kg or 9 times the MRHD as mg/m^2) prior to mating, except for a small reduction in the number of offspring per litter.

Pregnancy Category B

Reproduction studies in rats and rabbits during organogenesis at 100 and 22 times the MRHD as mg/kg (9 and 7 times the MRHD as mg/m^2), respectively, did not reveal any teratogenic potential associated with sotalol HCl. In rabbits, a high dose of sotalol HCl (160 mg/kg/day) at 16 times the MRHD as mg/kg (6 times the MRHD as mg/m^2) produced a slight increase in fetal death likely due to maternal toxicity. Eight times the maximum dose (80 mg/kg/day or 3 times the MRHD as mg/m^2) did not result in an increased incidence of fetal deaths. In rats, 1000 mg/kg/day sotalol HCl, 100 times the MRHD (18 times the MRHD as mg/m^2), increased the number of early resorptions, while at 14 times the maximum dose (2.5 times the MRHD as mg/m^2), no increase in early resorptions was noted. However, animal reproduction studies are not always predictive of human response.

Although there are no adequate and well-controlled studies in pregnant women, sotalol HCl has been shown to cross the placenta, and is found in amniotic fluid. There has been a report of subnormal birth weight with sotalol. Therefore, Sotalol AF should be used during pregnancy only if the potential benefit outweighs the potential risk.

Nursing Mothers

Sotalol is excreted in the milk of laboratory animals and has been reported to be present in human milk. Because of the potential for adverse reactions in nursing infants from Sotalol AF, a decision should be made whether to discontinue nursing or to discontinue the drug, taking into account the importance of the drug to the mother.

Pediatric Use

The safety and effectiveness of Sotalol AF in children have not been established. However, the Class III electrophysiologic and beta-blocking effects, the pharmacokinetics, and the relationship between the effects (QTc interval and resting heart rate) and drug concentrations have been evaluated in children aged between 3 days and 12 years old. (See CLINICAL PHARMACOLOGY.)

ADVERSE REACTIONS

Adverse events that are clearly related to Sotalol AF are those which are typical of its Class II (beta-blocking) and Class III (cardiac action potential duration prolongation) effects. The common documented beta-blocking adverse events (bradycardia, dyspnea, and fatigue) and Class III effects (QT interval prolongation) are dose related.

In a pooled clinical trial population consisting of four placebo-controlled studies with 275 patients with AFIB/AFL treated with 160 to 320 mg doses of Sotalol AF, the following adverse events were reported at a rate of 2% or more in the 160 to 240 mg treated patients and greater than the rate in placebo patients (See Table 8). The data are presented by incidence of events in the Sotalol AF and placebo groups by body system and daily dose. No significant irreversible non-cardiac end-organ toxicity was observed.

Table 8 Incidence (%) of Common Adverse Events (≥2% in the 160 to 240 mg group and more frequent than on placebo) in Four Placebo-Controlled Studies of Patients with AFIB/AFL
 | Placebo | Sotalol AF; Total Daily Dose
Body System/; Adverse Event (Preferred Term) | N=282 | 160 to 240; N=153 | >240 to 320; N=122
CARDIOVASCULAR
Abnormality ECG | 0.4 | 3.3 | 2.5
Angina Pectoris | 1.1 | 2.0 | 1.6
Bradycardia | 2.5 | 13.1 | 12.3
Chest Pain Cardiac/Non-Anginal | 4.6 | 4.6 | 2.5
Disturbance Rhythm Atrial | 2.1 | 2.0 | 1.6
Disturbance Rhythm Subjective | 9.9 | 9.8 | 7.4
GASTROINTESTINAL
Appetite Decreased | 0.4 | 2.0 | 1.6
Diarrhea | 2.1 | 5.2 | 5.7
Distention Abdomen | 0.4 | 0.7 | 2.5
Dyspepsia/Heartburn | 1.8 | 2.0 | 2.5
Nausea/Vomiting | 5.3 | 7.8 | 5.7
Pain Abdomen | 2.5 | 3.9 | 2.5
GENERAL
Fatigue | 8.5 | 19.6 | 18.9
Fever | 0.7 | 0.7 | 3.3
Hyperhidrosis | 3.2 | 5.2 | 4.9
Influenza | 0.4 | 2.0 | 0.8
Sensation Cold | 0.7 | 2.0 | 2.5
Weakness | 3.2 | 5.2 | 4.9
MUSCULOSKELETAL/CONNECTIVE TISSUE
Pain Chest Musculoskeletal | 1.4 | 2.0 | 2.5
Pain Musculoskeletal | 2.8 | 2.6 | 4.1
NERVOUS SYSTEM
Dizziness | 12.4 | 16.3 | 13.1
Headache | 5.3 | 3.3 | 11.5
Insomnia | 1.1 | 2.6 | 4.1
RESPIRATORY
Cough | 2.5 | 3.3 | 2.5
Dyspnea | 7.4 | 9.2 | 9.8
Infection Upper Respiratory | 1.1 | 2.6 | 3.3
Tracheobronchitis | 0.7 | 0.7 | 3.3
SPECIAL SENSES
Disturbance Vision | 0.7 | 2.6 | 0.8

Overall, discontinuation because of unacceptable adverse events was necessary in 17% of the patients, and occurred in 10% of patients less than two weeks after starting treatment. The most common adverse events leading to discontinuation of Sotalol AF were: fatigue 4.6%, bradycardia 2.4%, proarrhythmia 2.2%, dyspnea 2%, and QT interval prolongation 1.4%.

In clinical trials involving 1292 patients with sustained VT/VF, the common adverse events (occurring in ≥2% of patients) were similar to those described for the AFIB/AFL population.

Occasional reports of elevated serum liver enzymes have occurred with sotalol therapy but no cause and effect relationship has been established. One case of peripheral neuropathy which resolved on discontinuation of sotalol and recurred when the patient was rechallenged with the drug was reported in an early dose tolerance study. Elevated blood glucose levels and increased insulin requirements can occur in diabetic patients.

In an unblinded multicenter trial of 25 patients with SVT and/or VT receiving daily doses of 30, 90 and 210 mg/m^2 with dosing every 8 hours for a total of 9 doses, no Torsades de Pointes or other serious new arrhythmias were observed. One (1) patient, receiving 30 mg/m^2 daily, was discontinued because of increased frequency of sinus pauses/bradycardia. Additional cardiovascular AEs were seen at the 90 and 210 mg/m^2 daily dose levels. They included QT prolongations (2 patients), sinus pauses/bradycardia (1 patient), increased severity of atrial flutter and reported chest pain (1 patient). Values for QTc ≥525 msec were seen in 2 patients at the 210 mg/m^2 daily dose level. Serious adverse events including death, Torsades de Pointes, other proarrhythmias, high-degree A-V blocks and bradycardia have been reported in infants and/or children.

Potential Adverse Effects

Foreign marketing experience with sotalol hydrochloride shows an adverse experience profile similar to that described above from clinical trials. Voluntary reports since introduction also include rare reports of: emotional liability, slightly clouded sensorium, incoordination, vertigo, paralysis, thrombocytopenia, eosinophilia, leukopenia, photosensitivity reaction, fever, pulmonary edema, hyperlipidemia, myalgia, pruritis, alopecia.

The oculomucocutaneous syndrome associated with the beta-blocker practolol has not been associated with Sotalol AF during investigational use and foreign marketing experience.

OVERDOSAGE

Intentional or accidental overdosage with sotalol has rarely resulted in death.

Symptoms and Treatment of Overdosage

The most common signs to be expected are bradycardia, congestive heart failure, hypotension, bronchospasm and hypoglycemia. In cases of massive intentional overdosage (2 to 16 grams) of sotalol the following clinical findings were seen: hypotension, bradycardia, cardiac asystole, prolongation of QT interval, Torsade de Pointes, ventricular tachycardia, and premature ventricular complexes. If overdosage occurs, therapy with Sotalol AF should be discontinued and the patient observed closely. Because of the lack of protein binding, hemodialysis is useful for reducing sotalol plasma concentrations. Patients should be carefully observed until QT intervals are normalized and the heart rate returns to levels >50 bpm. The occurrence of hypotension following an overdose may be associated with an initial slow drug elimination phase (half life of 30 hours) thought to be due to a temporary reduction of renal function caused by the hypotension. In addition, if required, the following therapeutic measures are suggested:

Bradycardia or Cardiac Asystole: Atropine, another anticholinergic drug, a beta-adrenergic agonist or transvenous cardiac pacing.

Heart Block: (second and third degree) transvenous cardiac pacemaker.

Hypotension: (depending on associated factors) epinephrine rather than isoproterenol or norepinephrine may be useful.

Bronchospasm: Aminophylline or aerosol beta-2-receptor stimulant.

Torsade de Pointes: DC cardioversion, transvenous cardiac pacing, epinephrine, magnesium sulfate.

DOSAGE AND ADMINISTRATION

Dosing and Administration in Adults

- Therapy with Sotalol AF must be initiated (and, if necessary, titrated) in a setting that provides continuous electrocardiographic (ECG) monitoring and in the presence of personnel trained in the management of serious ventricular arrhythmias. Patients should continue to be monitored in this way for a minimum of 3 days on the maintenance dose. In addition, patients should not be discharged within 12 hours of electrical or pharmacological conversion to normal sinus rhythm.
- The QT interval is used to determine patient eligibility for Sotalol AF treatment and for monitoring safety during treatment. The baseline QT interval must be ≤450 msec in order for a patient to be started on Sotalol AF therapy. During initiation and titration, the QT interval should be monitored 2 to 4 hours after each dose. If the QT interval prolongs to 500 msec or greater, the dose must be reduced or the drug discontinued.
- The dose of Sotalol AF must be individualized according to calculated creatinine clearance. In patients with a creatinine clearance >60 mL/min Sotalol AF is administered twice daily (BID) while in those with a creatinine clearance between 40 and 60 mL/min, the dose is administered once daily (QD). In patients with a creatinine clearance less than 40 mL/min Sotalol AF is contraindicated. The recommended initial dose of Sotalol AF is 80 mg and is initiated as shown in the dosing algorithm described below. The 80 mg dose can be titrated upward to 120 mg during initial hospitalization or after discharge on 80 mg in the event of recurrence, by rehospitalization and repeating the same steps used during the initiation of therapy (see Upward Titration of Dose).
- Patients with atrial fibrillation should be anticoagulated according to usual medical practice. Hypokalemia should be corrected before initiation of Sotalol AF therapy (see WARNINGS, Ventricular Arrhythmia).
- Patients to be discharged on Sotalol AF therapy from an in-patient setting should have an adequate supply of Sotalol AF, to allow uninterrupted therapy until the patient can fill a Sotalol AF prescription.

Initiation of Sotalol AF Therapy

Step 1. Electrocardiographic assessment: Prior to administration of the first dose, the QT interval must be determined using an average of 5 beats. If the baseline QT is greater than 450 msec (JT ≥330 msec if QRS over 100 msec), Sotalol AF is contraindicated.

Step 2. Calculation of creatinine clearance: Prior to the administration of the first dose, the patient's creatinine clearance should be calculated using the following formula:

creatinine clearance (male) = | (140-age)x body weight in kg
creatinine clearance (male) = | 72 x serum creatinine (mg/dL)
creatinine clearance (female) = | (140-age)x body weight in kg x 0.85
creatinine clearance (female) = | 72 x serum creatinine (mg/dL)

When serum creatinine is given in μmol/L, divide the value by 88.4 (1 mg/dL = 88.4 μmol/L).

Step 3. Starting Dose: The starting dose of Sotalol AF is 80 mg twice daily (BID) if the creatinine clearance is >60 mL/min, and 80 mg once daily (QD) if the creatinine clearance is 40 to 60 mL/min. If the creatinine clearance is <40 mL/min Sotalol AF is contraindicated.

Step 4. Administer the appropriate daily dose of Sotalol AF and begin continuous ECG monitoring with QT interval measurements 2 to 4 hours after each dose.

Step 5. If the 80 mg dose level is tolerated and the QT interval remains <500 msec after at least 3 days (after 5 or 6 doses if patient receiving QD dosing), the patient can be discharged. Alternatively, during hospitalization, the dose can be increased to 120 mg bid and the patient followed for 3 days on this dose (followed for 5 or 6 doses if patient receiving QD doses).

The steps described above are summarized in the following diagram:

Place Patient on Telemetry

Check Baseline QT

If QT >450 msec Sotalol AF is CONTRAINDICATED

If QT ≤450 msec, proceed

Calculate Creatine Clearance (Clcr)

If Clcr is <40 mL/min Sotalol AF is CONTRAINDICATED

If Clcr is 40 to 60 mL/min start Sotalol AF 80 mg QD

If Clcr is >60 mL/min start Sotalol AF 80 mg BID

Monitor QT 2 to 4 hours after each dose.

If QT ≥500 msec discontinue Sotalol AF

If QT <500 msec after 3 days (after 5th or 6th dose if patient receiving QD dosing)

discharge patient on current treatment. Alternatively, during hospitalization, the dose can be increased to 120 mg BID and the patient followed for 3 days on this dose (followed for 5 or 6 doses if patient receiving QD doses).

Upward Titration of Dose

If the 80 mg dose level (given BID or QD depending upon the creatinine clearance) does not reduce the frequency of relapses of AFIB/AFL and is tolerated without excessive QT interval prolongation (i.e., ≥520 msec), the dose level may be increased to 120 mg (BID or QD depending upon the creatinine clearance). As proarrhythmic events can occur not only at initiation of therapy, but also with each upward dosage adjustment, Steps 2 through 5 used during initiation of Sotalol AF therapy should be followed when increasing the dose level. In the U.S. multicenter dose-response study, the 120 mg dose (BID or QD) was found to be the most effective in prolonging the time to ECG documented symptomatic recurrence of AFIB/AFL. If the 120 mg dose does not reduce the frequency of early relapse of AFIB/AFL and is tolerated without excessive QT interval prolongation (≥520 msec), an increase to 160 mg (BID or QD depending upon the creatinine clearance), can be considered. Steps 2 through 5 used during the initiation of therapy should be used again to introduce such an increase.

Maintenance of Sotalol AF Therapy

Renal function and QT should be re-evaluated regularly if medically warranted. If QT is 520 msec or greater (JT 430 msec or greater if QRS is > 100 msec), the dose of Sotalol AF therapy should be reduced and patients should be carefully monitored until QT returns to less than 520 msec. If the QT interval is ≥520 msec while on the lowest maintenance dose level (80 mg) the drug should be discontinued. If renal function deteriorates, reduce the daily dose in half by administering the drug once daily as described in Initiation of Sotalol AF Therapy, Step 3.

Special Considerations

The maximum recommended dose in patients with a calculated creatinine clearance greater than 60 mL/min is 160 mg BID, doses greater than 160 mg BID have been associated with an increased incidence of Torsade de Pointes and are not recommended.

A patient who misses a dose should NOT double the next dose. The next dose should be taken at the usual time.

Dosing and Administration in Children

As in adults the following precautionary measures should be considered when initiating sotalol treatment in children: initiation of treatment in the hospital after appropriate clinical assessment; individualized regimen as appropriate; gradual increase of doses if required; careful assessment of therapeutic response and tolerability; and frequent monitoring of the QTc interval and heart rate.

For children aged about 2 years and greater

For children aged about 2 years and greater, with normal renal function, doses normalized for body surface area are appropriate for both initial and incremental dosing. Since the Class III potency in children (see CLINICAL PHARMACOLOGY) is not very different from that in adults, reaching plasma concentrations that occur within the adult dose range is an appropriate guide. From pediatric pharmacokinetic data the following is recommended.

For initiation of treatment, 30 mg/m^2 three times a day (90 mg/m^2 total daily dose) is approximately equivalent to the initial 160 mg total daily dose for adults. Subsequent titration to a maximum of 60 mg/m^2 (approximately equivalent to the 360 mg total daily dose for adults) can then occur. Titration should be guided by clinical response, heart rate and QTc, with increased dosing being preferably carried out in-hospital. At least 36 hours should be allowed between dose increments to attain steady-state plasma concentrations of sotalol in patients with age-adjusted normal renal function.

For children aged about 2 years or younger

For children aged about 2 years or younger, the above pediatric dosage should be reduced by a factor that depends heavily upon age, as shown in the following graph, age plotted on a logarithmic scale in months.

For a child aged 20 months, the dosing suggested for children with normal renal function aged 2 years or greater should be multiplied by about 0.97; the initial starting dose would be (30 X 0.97)=29.1 mg/m^2, administered three times daily. For a child aged 1 month, the starting dose should be multiplied by 0.68; the initial starting dose would be (30 X 0.68)=20 mg/m^2, administered three times daily. For a child aged about 1 week, the initial starting dose should be multiplied by 0.3; the starting dose would be (30 X 0.3)=9 mg/m^2. Similar calculations should be made for increased doses as titration proceeds. Since the half-life of sotalol decreases with decreasing age (below about 2 years), time to steady-state will also increase. Thus, in neonates the time to steady-state may be as long as a week or longer.

In all children, individualization of dosage is required. As in adults Sotalol AF (sotalol hydrochloride) should be used with particular caution in children if the QTc is greater than 500 msec on therapy and serious consideration should be given to reducing the dose or discontinuing therapy when QTc exceeds 550 msec.

The use of Sotalol AF in children with renal impairment has not been investigated. Sotalol elimination is predominantly via the kidney in the unchanged form. Use of sotalol in any age group with decreased renal function should be at lower doses or at increased intervals between doses. Monitoring of heart rate and QTc is more important and it will take much longer to reach steady-state with any dose and/or frequency of administration.

Transfer to Sotalol AF from Sotalol

Patients with a history of symptomatic AFIB/AFL who are currently receiving sotalol the maintenance of normal sinus should be transferred to Sotalol AF because of the significant differences in labeling (i.e., patient package insert, dosing administration, and safety information).

Transfer to Sotalol AF from Other Antiarrhythmic Agents

Before starting Sotalol AF, previous antiarrhythmic therapy should generally be withdrawn under careful monitoring for a minimum of 2 to 3 plasma half-lives if the patient's clinical condition permits (see Drug Interactions). Treatment has been initiated in some patients receiving I.V. lidocaine without ill effect. After discontinuation of amiodarone, Sotalol AF should not be initiated until the QT interval is normalized (see WARNINGS).

Preparation of Extemporaneous Oral Solution
Sotalol AF Syrup 5 mg/mL can be compounded using Simple Syrup containing sucrose 85%w/v, purified water, citric acid and 0.1% Methyl Paraben as preservative:
1. Measure 120 mL of Simple Syrup
2. Transfer the syrup to a 150 mL amber plastic (polyethylene terephthalate [PET]) prescription bottle. NOTE: An oversized bottle is used to allow for a headspace, so that there will be more effective mixing during shaking of the bottle.
3. Add five (5) Sotalol AF 120 mg tablets to the bottle. These tablets are added intact; it is not necessary to crush the tablets. NOTE: The addition of the tablets can also be done first. The tablets can also be crushed if preferred. If the tablets are crushed, care should be taken to transfer the entire quantity of tablet powder into the bottle containing the syrup.
4. Shake the bottle to wet the entire surface of the tablets. If the tablets have been crushed, shake the bottle until the endpoint is achieved.
5. Allow the tablets to hydrate for approximately two hours.
6. After at least two hours have elapsed, shake the bottle intermittently over the course of at least another two hours until the tablets are completely disintegrated. NOTE: The tablets can be allowed to hydrate overnight to simplify the disintegration process.

The endpoint is achieved when a dispersion of fine particles in the syrup is obtained.

This compounding procedure results in a solution containing 5 mg/mL of sotalol HCl. The fine solid particles are the water-insoluble inactive ingredients of the tablets.

This extemporaneously prepared oral solution of sotalol HCl (with suspended inactive particles) must be shaken well prior to administration. This is to ensure that the amount of inactive solid particles per dose remains constant throughout the duration of use.

Stability studies indicate that the suspension is stable when stored at controlled room temperature (15° to 30°C/59° to 86°F) and ambient humidity for three (3) months.

HOW SUPPLIED

Sotalol Hydrochloride Tablets, USP (AF) are presented as follows:

For 80 mg strength: White to off-white colored, capsule shaped, scored tablets debossed 'B107' on one side and scored on the other side.

For 120 mg strength: White to off-white colored, capsule shaped, scored tablets debossed 'B108' on one side and scored on the other side.

For 160 mg strength: White to off-white colored, capsule shaped, scored tablets debossed 'B109' on one side and scored on the other side.

Sotalol Hydrochloride Tablets, USP (AF) are available as follows:

80 mg strength,
NDC 76385-125-01 in bottle of 100 and
NDC 76385-125-50 in bottle of 500

120 mg strength,
NDC 76385-126-01 in bottle of 100 and
NDC 76385-126-50 in bottle of 500

160 mg strength,
NDC 76385-127-01 in bottle of 100 and
NDC 76385-127-50 in bottle of 500

Store at 25°C (77°F); excursions permitted to 15°C to 30°C (59°F to 86°F) [See USP Controlled Room Temperature].

To report SUSPECTED ADVERSE REACTIONS, contact Beximco Pharmaceuticals USA Inc. at 877-372-6093 or FDA at 1-800-FDA-1088 or www.fda.gov/medwatch.

Manufactured for
Beximco Pharmaceuticals USA Inc.4110 Regal Oaks Drive, P.O. Box 1060, Suwanee, GA 30024, USA

Distributed by:
Bayshore Pharmaceuticals LLC
Short Hills, NJ 07078

Betapace is a registered trademark of Bayer Healthcare Inc.

3020007209 060119

PATIENT INFORMATION

What You Should Know About Sotalol AF

(generic name: sotalol hydrochloride)

BOXED WARNING

This summary contains important patient information that has been reviewed and approved by the U.S. Food and Drug Administration. This summary is not meant to take the place of your doctor's instructions. Read this patient information carefully before you start taking Sotalol AF. Each time you get a refill, you will receive patient information. Be sure to read it because it may contain new information that you need to know.

What is the most important information I should know about Sotalol AF?

Because you have irregular heartbeats (atrial fibrillation) that are troublesome to you, Sotalol AF has been prescribed to help your heart to beat in a more normal way. However, in some patients Sotalol AF can cause a different type of abnormal heartbeat that can be dangerous, and in rare instances can even cause death. You may feel this different type of abnormal heartbeat as a fast beating of the heart with lightheadedness and fainting. The possibility of this different type of abnormal heartbeat is the reason you and your doctor have discussed whether your symptoms are troublesome enough for you to start taking Sotalol AF.

Clinical studies using Sotalol AF have shown that the most important way to decrease your chance of getting this different type of dangerous abnormal heartbeat is for you to take the dose of Sotalol AF that is right for you. If this abnormal heartbeat occurs, it usually happens during the first few days of treatment. This is why you should be started on Sotalol AF in a hospital or another place where your heartbeat can be watched closely by health care professionals for the first few days. They can help you if problems occur. When Sotalol AF is started this way, this different type of abnormal heartbeat is rare and the hospital staff is there to treat it.

It is important that when you go home, you take the exact dose the doctor prescribed for you. At any time while you are taking Sotalol AF, watch for signs that you may be getting this different type of abnormal heartbeat and call your doctor if they occur. Call your doctor right away if you:

- faint,
- become dizzy, or
- have fast heartbeats.

If you cannot reach your doctor, go to the nearest hospital emergency room. Take your Sotalol AF tablets with you and show them to the doctor or nurse.

Also, call your doctor right away if you have any of the following conditions:

- severe diarrhea
- unusual sweating
- vomiting
- less appetite than normal, or
- more thirst than normal.

These are conditions that will make you more likely to get the different type of abnormal heartbeat.

If you take Sotalol AF with certain other medicines, you will increase your chance of getting this different type of abnormal heartbeat. These medicines are listed below under "Who should not take Sotalol AF?"

Once your doctor finds the right dose for you, always take that exact amount of Sotalol AF. Never take an extra dose and never skip a dose of Sotalol AF.

What is Sotalol AF?

Sotalol AF is a medicine that is given to patients with atrial fibrillation (irregular heartbeats). Atrial fibrillation happens when certain parts of the heart (the chambers known as atria) beat too fast or irregularly. When this happens, your heart cannot pump blood through your body as well as it should. This may make you feel weak and tired, or get out of breath easily. You may get an uncomfortable feeling in your chest and "fluttering" or "palpitations." Atrial fibrillation can be changed back (converted) to normal heart rhythm by an electric shock or by using certain medicines. However, atrial fibrillation can return. Sotalol AF may help your heart stay beating regularly for a longer period of time.

This information about Sotalol AF was developed to ensure that you and your doctor get the right information about your type of irregular heartbeats. Consult your doctor before you accept any other sotalol product that does not provide this patient information.

Who should not take Sotalol AF?

Sotalol AF is not for everyone with irregular heartbeats (atrial fibrillation). This is why you and your doctor need to discuss the benefits and risks of Sotalol AF and whether your symptoms are troublesome enough for you to start taking Sotalol AF.

Do not take Sotalol AF if you:

- have serious kidney problems or are on kidney dialysis;
- have lung disease causing shortness of breath (such as asthma, chronic bronchitis or emphysema);
- have symptoms of heart failure (such as shortness of breath when you exercise or are physically active and swelling of the ankles or legs);
- have a very slow heart beat and do not have an implanted artificial pacemaker;

Taking certain other medicines with Sotalol AF can increase the chance that you will get the dangerous abnormal heartbeat discussed in "What is the most important information I should know about Sotalol AF?" These include medicines used to treat abnormal heart rhythms and some other heart problems as well as medicines used to treat depression and other mental problems, night-time heartburn, asthma and infections. Therefore, you should be sure to tell your health care provider about all prescription and non-prescription medicines you are taking, as well as vitamins, dietary supplements, and any natural or herbal remedies. In addition, tell your doctor about any problems you have with your heart or kidneys.

If you are pregnant, you should know that there is no information about the safety of Sotalol AF in pregnant women. Some reports indicate that Sotalol AF is passed into the breast milk. Women who are taking Sotalol AF should not breast feed a child.

How should I take Sotalol AF?

Your doctor will start you on Sotalol AF in the hospital and will check your heart rhythm for the first 2 or more days of treatment. This will allow your doctor to find the right dose for you. Always take the exact amount your doctor prescribes. Never change your Sotalol AF dose unless your doctor tells you to. Your doctor will do regular tests to check that the amount you're taking is still right for you.

Keep taking your Sotalol AF until your doctor tells you to stop. Keep taking it even if you feel fine. However, never take an extra dose of Sotalol AF even if you do not feel well. When it is time to stop taking Sotalol AF, your doctor will give you instructions on how to gradually reduce your dose over a period of 1 to 2 weeks.

You may take Sotalol AF with or without food. However, it is important to take Sotalol AF at the same time every day. This gives your heart a steady supply of the medicine. It might be helpful to take Sotalol AF at the same time as something you regularly do every day.

If you are taking an antacid containing aluminum or magnesium to treat heartburn or upset stomach wait at least 2 hours after your dose of Sotalol AF before you take the antacid.

Never try to make up for a missed dose of Sotalol AF. You could increase your chance of getting the different type of abnormal heartbeat. If you miss taking a dose of Sotalol AF, just take your normal amount at the next scheduled time.

If you take more Sotalol AF than you should have, call your doctor right away. If you cannot reach your doctor, go to the nearest hospital emergency room. Take your Sotalol AF tablets with you to show to the doctor or nurse.

What should I avoid while taking Sotalol AF?

Certain other medicines taken with Sotalol AF may increase the chance that you will get the dangerous abnormal heartbeat (see "Who should not take Sotalol AF?"). Do not take Sotalol AF with these medicines. Before you start taking Sotalol AF tell your doctor about all prescription and non-prescription medicines you are taking (see also "Who should not take Sotalol AF?"). Once you begin taking Sotalol AF, do not start taking any new medicines until you check with your doctor.

Carry a list of all the medicines and supplements you take. If you have to go to the hospital or are treated by new or different health care providers, tell them you are taking Sotalol AF and show them the list of other medicines you take. They need this information to make sure your medicines are safe to take at the same time.

Tell your doctor or dentist you are taking Sotalol AF before you have an operation or dental surgery. Sotalol AF can affect how well some anesthetics work.

What are the possible side effects of Sotalol AF?

Sotalol AF's most serious side effect, a different type of dangerous abnormal heartbeat, is discussed in "What is the most important information I should know about Sotalol AF?" Dangerous abnormal heartbeats happen rarely. But they can be serious and, in rare instances, can even cause death.

Sotalol AF's most common side effects are tiredness, slow rate, shortness of breath, and dizziness. Sotalol AF can also cause other side effects. If you are concerned about these or any other side effects, ask your doctor.

Important points about Sotalol AF

Sotalol AF can help you best if you take it as your doctor has prescribed it.

- Take your medicine every day as prescribed.
- Do not miss doses or take extra doses.
- Call your doctor right away if you feel new fast heartbeats with lightheadedness and fainting. These can be serious and in rare instances can even cause death.
- Do not take Sotalol AF if you have serious kidney problems, lung disease causing shortness of breath, symptoms of heart failure.
- Tell your doctor and pharmacist the name of all medications (prescription, non-prescription, and natural/herbal remedies) you are taking.
- Do not start taking any other medicines without telling your doctor.
- Go for all your regular checkups.
- Get your refills on time.
- Do not stop taking Sotalol AF until your doctor tells you to stop.

This leaflet provides a summary of information about Sotalol AF. Your doctor or pharmacist has a longer leaflet written for healthcare professionals that you can ask to read. Sotalol AF was prescribed for your particular condition. Do not use it for another condition or give it to others.

To report SUSPECTED ADVERSE REACTIONS, contact Beximco Pharmaceuticals USA Inc. at 877-372-6093 or FDA at 1-800-FDA-1088 or www.fda.gov/medwatch.

Manufactured for:
Beximco Pharmaceuticals USA Inc.
4110 Regal Oaks Drive, P.O. Box 1060, Suwanee, GA 30024, USA

Manufactured by:
Beximco Pharmaceuticals Limited
126, Kathaldia, Tongi, Gazipur, 1711, Bangladesh

Distributed by:
Bayshore Pharmaceuticals LLC
Short Hills, NJ 07078

3020007209 060119

PRINCIPAL DISPLAY PANEL - 80 mg container label

NDC 76385-125-01

100 Tablets

Sotalol Hydrochloride Tablets, USP (AF)

80 mg Rx only

Distributed by:
Bayshore Pharmaceuticals LLC
Short Hills, NJ 07078

Manufactured by
BEXIMCO PHARMACEUTICALS LTD.
126, Kathaldia, Tongi, Gazipur, 1711, Bangladesh

PRINCIPAL DISPLAY PANEL - 120 mg container label

NDC 76385-126-01

100 Tablets

Sotalol Hydrochloride Tablets, USP (AF)

120 mg Rx only

Distributed by:
Bayshore Pharmaceuticals LLC
Short Hills, NJ 07078

Manufactured by
BEXIMCO PHARMACEUTICALS LTD.
126, Kathaldia, Tongi, Gazipur, 1711, Bangladesh

PRINCIPAL DISPLAY PANEL - 160 mg container label

NDC 76385-127-01

100 Tablets

Sotalol Hydrochloride Tablets, USP (AF)

160 mg Rx only

Distributed by:
Bayshore Pharmaceuticals LLC
Short Hills, NJ 07078

Manufactured by
BEXIMCO PHARMACEUTICALS LTD.
126, Kathaldia, Tongi, Gazipur, 1711, Bangladesh